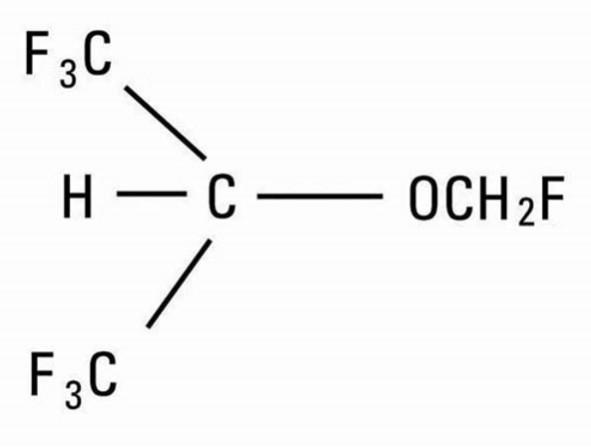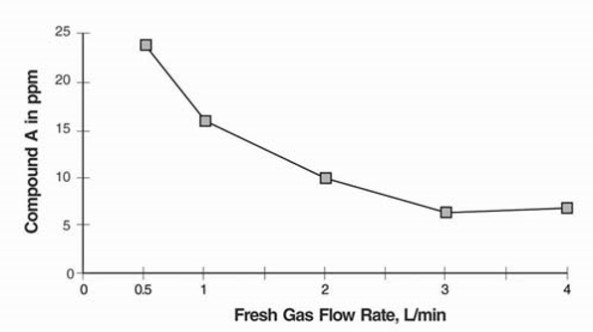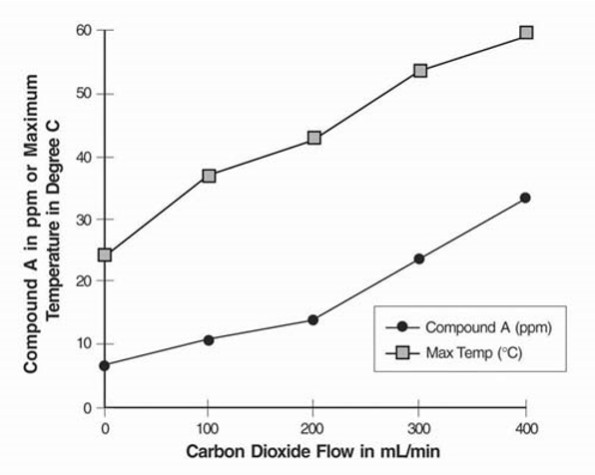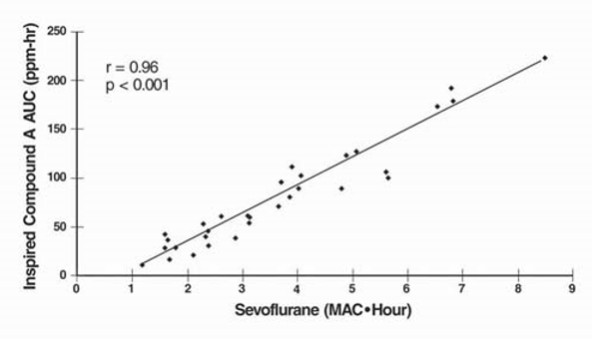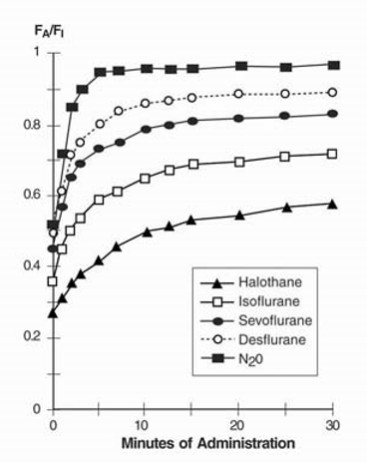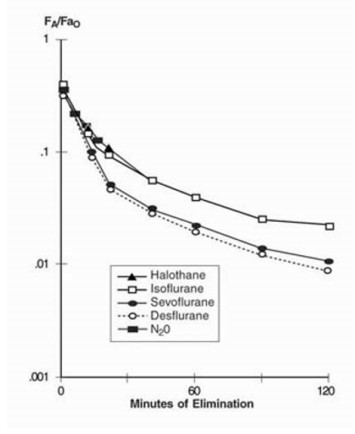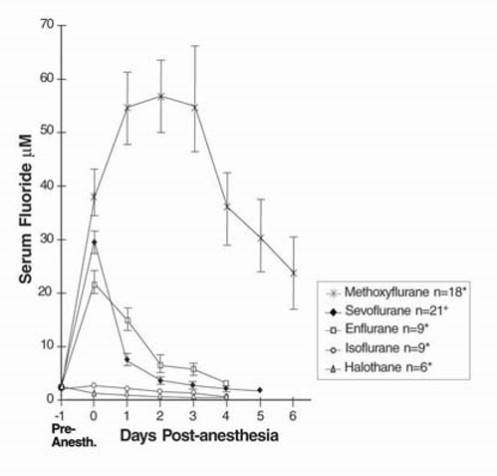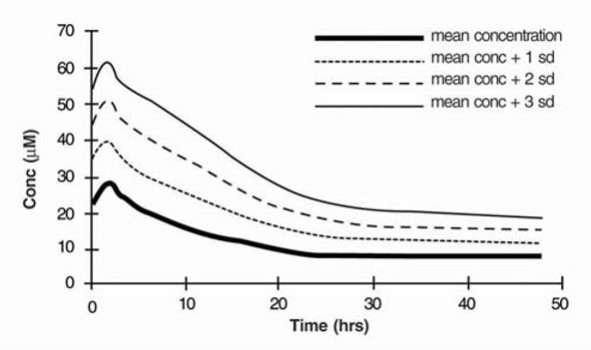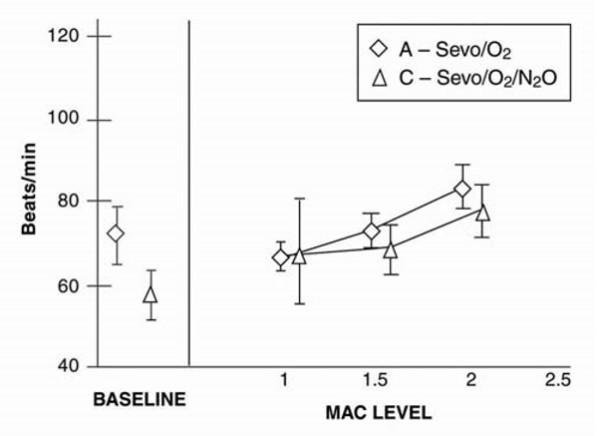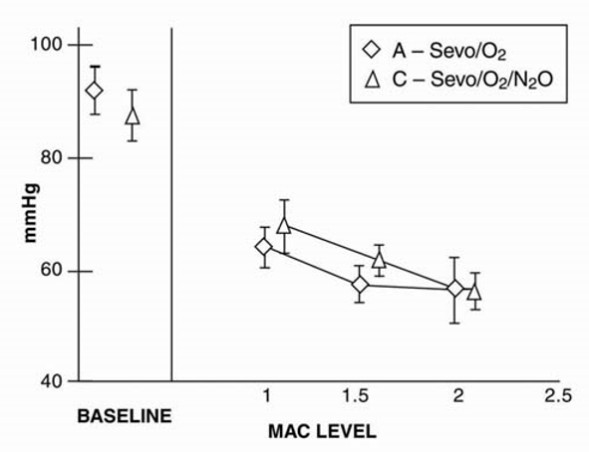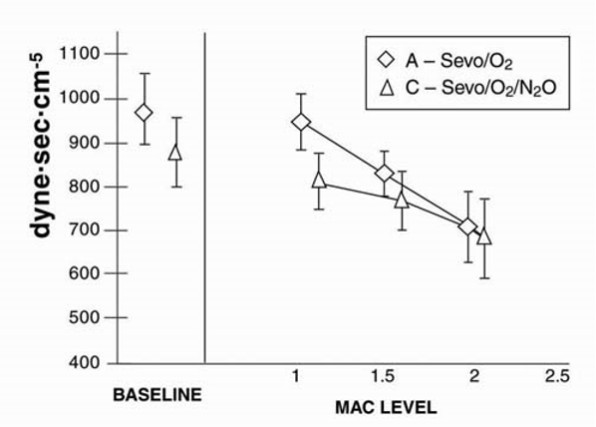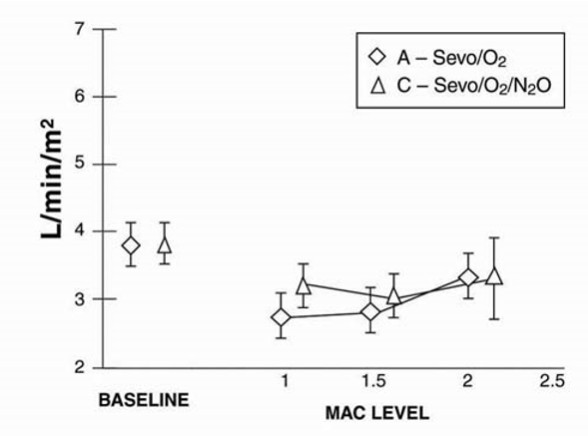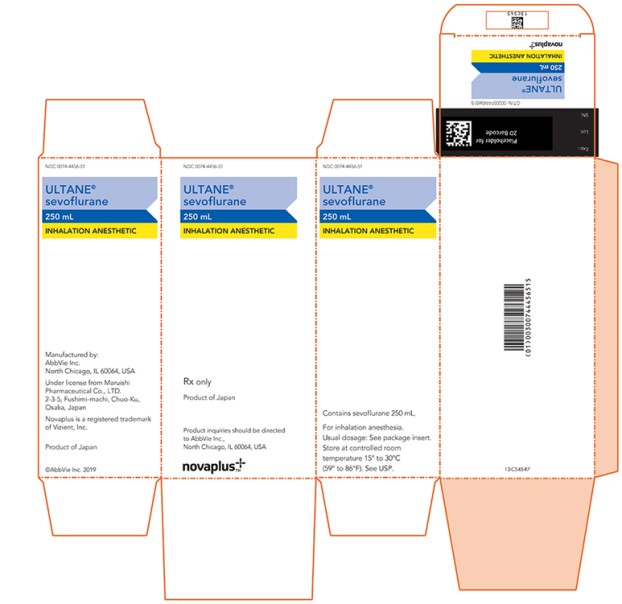 DRUG LABEL: Ultane
NDC: 0074-4456 | Form: LIQUID
Manufacturer: AbbVie Inc.
Category: prescription | Type: HUMAN PRESCRIPTION DRUG LABEL
Date: 20250212

ACTIVE INGREDIENTS: SEVOFLURANE 250 mL/250 mL

ULTANE®
(sevoflurane)
volatile liquid for inhalation
novaplus TM

DESCRIPTION

ULTANE (sevoflurane), volatile liquid for inhalation, a nonflammable and nonexplosive liquid administered by vaporization, is a halogenated general inhalation anesthetic drug. Sevoflurane is fluoromethyl 2,2,2,-trifluoro-1-(trifluoromethyl) ethyl ether and its structural formula is:

Sevoflurane, Physical Constants are:
Molecular weight | 200.05
Boiling point at 760 mm Hg | 58.6°C
Specific gravity at 20°C | 1.520 - 1.525
Vapor pressure in mm Hg | 157 mm Hg at 20°C
 | 197 mm Hg at 25°C
 | 317 mm Hg at 36°C

Distribution Partition Coefficients at 37°C:
Blood/Gas | 0.63 - 0.69
Water/Gas | 0.36
Olive Oil/Gas | 47 – 54
Brain/Gas | 1.15

Mean Component/Gas Partition Coefficients at 25°C for Polymers Used Commonly in Medical Applications:
Conductive rubber | 14.0
Butyl rubber | 7.7
Polyvinylchloride | 17.4
Polyethylene | 1.3

Sevoflurane is nonflammable and nonexplosive as defined by the requirements of International Electrotechnical Commission 601-2-13.

Sevoflurane is a clear, colorless, liquid containing no additives. Sevoflurane is not corrosive to stainless steel, brass, aluminum, nickel-plated brass, chrome-plated brass or copper beryllium. Sevoflurane is nonpungent. It is miscible with ethanol, ether, chloroform, and benzene, and it is slightly soluble in water. Sevoflurane is stable when stored under normal room lighting conditions according to instructions. No discernible degradation of sevoflurane occurs in the presence of strong acids or heat. When in contact with alkaline CO2 absorbents (e.g., Baralyme® and to a lesser extent soda lime) within the anesthesia machine, sevoflurane can undergo degradation under certain conditions. Degradation of sevoflurane is minimal, and degradants are either undetectable or present in non-toxic amounts when used as directed with fresh absorbents. Sevoflurane degradation and subsequent degradant formation are enhanced by increasing absorbent temperature increased sevoflurane concentration, decreased fresh gas flow and desiccated CO2 absorbents (especially with potassium hydroxide containing absorbents e.g., Baralyme).

Sevoflurane alkaline degradation occurs by two pathways. The first results from the loss of hydrogen fluoride with the formation of pentafluoroisopropenyl fluoromethyl ether, (PIFE, C4H2F6O), also known as Compound A, and trace amounts of pentafluoromethoxy isopropyl fluoromethyl ether, (PMFE, C5H6F6O), also known as Compound B. The second pathway for degradation of sevoflurane, which occurs primarily in the presence of desiccated CO2 absorbents, is discussed later.

In the first pathway, the defluorination pathway, the production of degradants in the anesthesia circuit results from the extraction of the acidic proton in the presence of a strong base (KOH and/or NaOH) forming an alkene (Compound A) from sevoflurane similar to formation of 2-bromo-2-chloro-1,1-difluoro ethylene (BCDFE) from halothane. Laboratory simulations have shown that the concentration of these degradants is inversely correlated with the fresh gas flow rate (See Figure 1).

Figure 1. Fresh Gas Flow Rate versus Compound A Levels in a Circle Absorber System

Since the reaction of carbon dioxide with absorbents is exothermic, the temperature increase will be determined by quantities of CO2 absorbed, which in turn will depend on fresh gas flow in the anesthesia circle system, metabolic status of the patient, and ventilation. The relationship of temperature produced by varying levels of CO2 and Compound A production is illustrated in the following in vitro simulation where CO2 was added to a circle absorber system.

Figure 2. Carbon Dioxide Flow versus Compound A and Maximum Temperature

Compound A concentration in a circle absorber system increases as a function of increasing CO2 absorbent temperature and composition (Baralyme producing higher levels than soda lime), increased body temperature, and increased minute ventilation, and decreasing fresh gas flow rates. It has been reported that the concentration of Compound A increases significantly with prolonged dehydration of Baralyme. Compound A exposure in patients also has been shown to rise with increased sevoflurane concentrations and duration of anesthesia. In a clinical study in which sevoflurane was administered to patients under low flow conditions for ≥ 2 hours at flow rates of 1 Liter/minute, Compound A levels were measured in an effort to determine the relationship between MAC hours and Compound A levels produced. The relationship between Compound A levels and sevoflurane exposure are shown in Figure 2a.

Figure 2a. ppm·hr versus MAC·hr at Flow Rate of 1 L/min

Compound A has been shown to be nephrotoxic in rats after exposures that have varied in duration from one to three hours. No histopathologic change was seen at a concentration of up to 270 ppm for one hour. Sporadic single cell necrosis of proximal tubule cells has been reported at a concentration of 114 ppm after a 3-hour exposure to Compound A in rats. The LC50 reported at 1 hour is 1050-1090 ppm (male-female) and, at 3 hours, 350-490 ppm (male-female).

An experiment was performed comparing sevoflurane plus 75 or 100 ppm Compound A with an active control to evaluate the potential nephrotoxicity of Compound A in non-human primates. A single 8-hour exposure of Sevoflurane in the presence of Compound A produced single-cell renal tubular degeneration and single-cell necrosis in cynomolgus monkeys. These changes are consistent with the increased urinary protein, glucose level and enzymic activity noted on days one and three on the clinical pathology evaluation. This nephrotoxicity produced by Compound A is dose and duration of exposure dependent.

At a fresh gas flow rate of 1 L/min, mean maximum concentrations of Compound A in the anesthesia circuit in clinical settings are approximately 20 ppm (0.002%) with soda lime and 30 ppm (0.003%) with Baralyme in adult patients; mean maximum concentrations in pediatric patients with soda lime are about half those found in adults. The highest concentration observed in a single patient with Baralyme was 61 ppm (0.0061%) and 32 ppm (0.0032%) with soda lime. The levels of Compound A at which toxicity occurs in humans is not known.

The second pathway for degradation of sevoflurane occurs primarily in the presence of desiccated CO2 absorbents and leads to the dissociation of sevoflurane into hexafluoroisopropanol (HFIP) and formaldehyde. HFIP is inactive, non-genotoxic, rapidly glucuronidated and cleared by the liver. Formaldehyde is present during normal metabolic processes. Upon exposure to a highly desiccated absorbent, formaldehyde can further degrade into methanol and formate. Formate can contribute to the formation of carbon monoxide in the presence of high temperature that can be associated with desiccated Baralyme®. Methanol can react with Compound A to form the methoxy addition product Compound B. Compound B can undergo further HF elimination to form Compounds C, D, and E.

Sevoflurane degradants were observed in the respiratory circuit of an experimental anesthesia machine using desiccated CO2 absorbents and maximum sevoflurane concentrations (8%) for extended periods of time (> 2 hours). Concentrations of formaldehyde observed with desiccated soda lime in this experimental anesthesia respiratory circuit were consistent with levels that could potentially result in respiratory irritation. Although KOH containing CO2 absorbents are no longer commercially available, in the laboratory experiments, exposure of sevoflurane to the desiccated KOH containing CO2 absorbent, Baralyme, resulted in the detection of substantially greater degradant levels.

CLINICAL PHARMACOLOGY

Sevoflurane is an inhalational anesthetic agent for use in induction and maintenance of general anesthesia. Minimum alveolar concentration (MAC) of sevoflurane in oxygen for a 40-year-old adult is 2.1%. The MAC of sevoflurane decreases with age (see DOSAGE AND ADMINISTRATION for details).

Pharmacokinetics

Uptake and Distribution

Solubility

Because of the low solubility of sevoflurane in blood (blood/gas partition coefficient @ 37°C = 0.63-0.69), a minimal amount of sevoflurane is required to be dissolved in the blood before the alveolar partial pressure is in equilibrium with the arterial partial pressure. Therefore, there is a rapid rate of increase in the alveolar (end-tidal) concentration (FA) toward the inspired concentration (FI) during induction.

Induction of Anesthesia

In a study in which seven healthy male volunteers were administered 70% N2O/30%O2 for 30 minutes followed by 1.0% sevoflurane and 0.6% isoflurane for another 30 minutes the FA/FI ratio was greater for sevoflurane than isoflurane at all time points. The time for the concentration in the alveoli to reach 50% of the inspired concentration was 4-8 minutes for isoflurane and approximately 1 minute for sevoflurane.

FA/FI data from this study were compared with FA/FI data of other halogenated anesthetic agents from another study. When all data were normalized to isoflurane, the uptake and distribution of sevoflurane was shown to be faster than isoflurane and halothane, but slower than desflurane. The results are depicted in Figure 3.

Recovery from Anesthesia

The low solubility of sevoflurane facilitates rapid elimination via the lungs. The rate of elimination is quantified as the rate of change of the alveolar (end-tidal) concentration following termination of anesthesia (FA), relative to the last alveolar concentration (FaO) measured immediately before discontinuance of the anesthetic. In the healthy volunteer study described above, rate of elimination of sevoflurane was similar compared with desflurane, but faster compared with either halothane or isoflurane. These results are depicted in Figure 4.

Figure 3. Ratio of Concentration of Anesthetic in Alveolar Gas to Inspired Gas

Figure 4. Concentration of Anesthetic in Alveolar Gas Following Termination of Anesthesia

Protein Binding

The effects of sevoflurane on the displacement of drugs from serum and tissue proteins have not been investigated. Other fluorinated volatile anesthetics have been shown to displace drugs from serum and tissue proteins in vitro. The clinical significance of this is unknown. Clinical studies have shown no untoward effects when sevoflurane is administered to patients taking drugs that are highly bound and have a small volume of distribution (e.g., phenytoin).

Metabolism

Sevoflurane is metabolized by cytochrome P450 2E1, to hexafluoroisopropanol (HFIP) with release of inorganic fluoride and CO2. Once formed HFIP is rapidly conjugated with glucuronic acid and eliminated as a urinary metabolite. No other metabolic pathways for sevoflurane have been identified. In vivo metabolism studies suggest that approximately 5% of the sevoflurane dose may be metabolized.

Cytochrome P450 2E1 is the principal isoform identified for sevoflurane metabolism and this may be induced by chronic exposure to isoniazid and ethanol. This is similar to the metabolism of isoflurane and enflurane and is distinct from that of methoxyflurane which is metabolized via a variety of cytochrome P450 isoforms. The metabolism of sevoflurane is not inducible by barbiturates. As shown in Figure 5, inorganic fluoride concentrations peak within 2 hours of the end of sevoflurane anesthesia and return to baseline concentrations within 48 hours post-anesthesia in the majority of cases (67%). The rapid and extensive pulmonary elimination of sevoflurane minimizes the amount of anesthetic available for metabolism.

Figure 5. Serum Inorganic Fluoride Concentrations for Sevoflurane and Other Volatile Anesthetics

Legend:
Pre-Anesth. = Pre-anesthesia

Elimination

Up to 3.5% of the sevoflurane dose appears in the urine as inorganic fluoride. Studies on fluoride indicate that up to 50% of fluoride clearance is nonrenal (via fluoride being taken up into bone).

Pharmacokinetics of Fluoride Ion

Fluoride ion concentrations are influenced by the duration of anesthesia, the concentration of sevoflurane administered, and the composition of the anesthetic gas mixture. In studies where anesthesia was maintained purely with sevoflurane for periods ranging from 1 to 6 hours, peak fluoride concentrations ranged between 12 µM and 90 µM. As shown in Figure 6, peak concentrations occur within 2 hours of the end of anesthesia and are less than 25 µM (475 ng/mL) for the majority of the population after 10 hours. The half-life is in the range of 15-23 hours.

It has been reported that following administration of methoxyflurane, serum inorganic fluoride concentrations > 50 µM were correlated with the development of vasopressin-resistant, polyuric, renal failure. In clinical studies with sevoflurane, there were no reports of toxicity associated with elevated fluoride ion levels.

Figure 6. Fluoride Ion Concentrations Following Administration of Sevoflurane (mean MAC = 1.27, mean duration = 2.06 hr) Mean Fluoride Ion Concentrations (n = 48)

Fluoride Concentrations After Repeat Exposure and in Special Populations

Fluoride concentrations have been measured after single, extended, and repeat exposure to sevoflurane in normal surgical and special patient populations, and pharmacokinetic parameters were determined.

Compared with healthy individuals, the fluoride ion half-life was prolonged in patients with renal impairment, but not in the elderly. A study in 8 patients with hepatic impairment suggests a slight prolongation of the half-life. The mean half-life in patients with renal impairment averaged approximately 33 hours (range 21-61 hours) as compared to a mean of approximately 21 hours (range 10-48 hours) in normal healthy individuals. The mean half-life in the elderly (greater than 65 years) approximated 24 hours (range 18-72 hours). The mean half-life in individuals with hepatic impairment was 23 hours (range 16-47 hours). Mean maximal fluoride values (Cmax) determined in individual studies of special populations are displayed below.

Table 1. Fluoride Ion Estimates in Special Populations Following Administration of Sevoflurane
 | n | Age (yr) | Duration (hr) | Dose (MAC·hr) | Cmax (µM)
PEDIATRIC PATIENTS
Anesthetic
Sevoflurane-O2 | 76 | 0-11 | 0.8 | 1.1 | 12.6
Sevoflurane-O2 | 40 | 1-11 | 2.2 | 3.0 | 16.0
Sevoflurane/N2O | 25 | 5-13 | 1.9 | 2.4 | 21.3
Sevoflurane/N2O | 42 | 0-18 | 2.4 | 2.2 | 18.4
Sevoflurane/N2O | 40 | 1-11 | 2.0 | 2.6 | 15.5
ELDERLY | 33 | 65-93 | 2.6 | 1.4 | 25.6
RENAL | 21 | 29-83 | 2.5 | 1.0 | 26.1
HEPATIC | 8 | 42-79 | 3.6 | 2.2 | 30.6
OBESE | 35 | 24-73 | 3.0 | 1.7 | 38.0
n = number of patients studied.

Pharmacodynamics

Changes in the depth of sevoflurane anesthesia rapidly follow changes in the inspired concentration.

In the sevoflurane clinical program, the following recovery variables were evaluated:

1. Time to events measured from the end of study drug:

- Time to removal of the endotracheal tube (extubation time)
- Time required for the patient to open his/her eyes on verbal command (emergence time)
- Time to respond to simple command (e.g., squeeze my hand) or demonstrates purposeful movement (response to command time, orientation time)

2. Recovery of cognitive function and motor coordination was evaluated based on:

- psychomotor performance tests (Digit Symbol Substitution Test [DSST], Trieger Dot Test)
- the results of subjective (Visual Analog Scale [VAS]) and objective (objective pain-discomfort scale [OPDS]) measurements
- time to administration of the first post-anesthesia analgesic medication
- assessments of post-anesthesia patient status

3. Other recovery times were:

- time to achieve an Aldrete Score of ≥ 8
- time required for the patient to be eligible for discharge from the recovery area, per standard criteria at site
- time when the patient was eligible for discharge from the hospital
- time when the patient was able to sit up or stand without dizziness

Some of these variables are summarized as follows:

Table 2. Induction and Recovery Variables for Evaluable Pediatric Patients in Two Comparative Studies: Sevoflurane versus Halothane
Time to End-Point (min) | Sevoflurane Mean ± SEM | Halothane Mean ± SEM
Induction | 2.0 ± 0.2 (n = 294) | 2.7 ± 0.2 (n = 252)
Emergence | 11.3 ± 0.7 (n = 293) | 15.8 ± 0.8 (n = 252)
Response to command | 13.7 ± 1.0 (n = 271) | 19.3 ± 1.1 (n = 230)
First analgesia | 52.2 ± 8.5 (n = 216) | 67.6 ± 10.6 (n = 150)
Eligible for recovery discharge | 76.5 ± 2.0 (n = 292) | 81.1 ± 1.9 (n = 246)
n = number of patients with recording of events.

Table 3. Recovery Variables for Evaluable Adult Patients in Two Comparative Studies: Sevoflurane versus Isoflurane
Time to Parameter: (min) | Sevoflurane Mean ± SEM | Isoflurane Mean ± SEM
Emergence | 7.7 ± 0.3 (n = 395) | 9.1 ± 0.3 (n = 348)
Response to command | 8.1 ± 0.3 (n = 395) | 9.7 ± 0.3 (n = 345)
First analgesia | 42.7 ± 3.0 (n = 269) | 52.9 ± 4.2 (n = 228)
Eligible for recovery discharge | 87.6 ± 5.3 (n = 244) | 79.1 ± 5.2 (n = 252)
n = number of patients with recording of recovery events.

Table 4. Meta-Analyses for Induction and Emergence Variables for Evaluable Adult Patients in Comparative Studies: Sevoflurane versus Propofol
Parameter | No. of Studies | Sevoflurane Mean ± SEM | Propofol Mean ± SEM
Mean maintenance anesthesia | 3 | 1.0 MAC·hr. ± 0.8 | 7.2 mg/kg/hr ± 2.6
exposure |  | (n = 259) | (n = 258)
Time to induction: (min) | 1 | 3.1 ± 0.18* | 2.2 ± 0.18**
 |  | (n = 93) | (n = 93)
Time to emergence: (min) | 3 | 8.6 ± 0.57 | 11.0 ± 0.57
 |  | (n = 255) | (n = 260)
Time to respond to command: (min) | 3 | 9.9 ± 0.60 | 12.1 ± 0.60
 |  | (n = 257) | (n = 260)
Time to first analgesia: (min) | 3 | 43.8 ± 3.79 | 57.9 ± 3.68
 |  | (n = 177) | (n = 179)
Time to eligibility for recovery | 3 | 116.0 ± 4.15 | 115.6 ± 3.98
discharge: (min) |  | (n = 257) | (n = 261)
* Propofol induction of one sevoflurane group = mean of 178.8 mg ± 72.5 SD (n = 165)
** Propofol induction of all propofol groups = mean of 170.2 mg ± 60.6 SD (n = 245)
n = number of patients with recording of events.

Cardiovascular Effects

Sevoflurane was studied in 14 healthy volunteers (18-35 years old) comparing sevoflurane-O2 (Sevo/O2) to sevoflurane-N2O/O2 (Sevo/N2O/O2) during 7 hours of anesthesia. During controlled ventilation, hemodynamic parameters measured are shown in Figures 7-10:

Figure 7. Heart Rate

Figure 8. Mean Arterial Pressure

Figure 9. Systemic Vascular Resistance

Figure 10. Cardiac Index

Sevoflurane is a dose-related cardiac depressant. Sevoflurane does not produce increases in heart rate at doses less than 2 MAC.

A study investigating the epinephrine induced arrhythmogenic effect of sevoflurane versus isoflurane in adult patients undergoing transsphenoidal hypophysectomy demonstrated that the threshold dose of epinephrine (i.e., the dose at which the first sign of arrhythmia was observed) producing multiple ventricular arrhythmias was 5 mcg/kg with both sevoflurane and isoflurane. Consequently, the interaction of sevoflurane with epinephrine appears to be equal to that seen with isoflurane.

Pharmacogenomics

RYR1 and CACNA1S are polymorphic genes, and multiple pathogenic variants have been associated with malignant hyperthermia susceptibility (MHS) in patients receiving volatile anesthetic agents, including sevoflurane. Case reports as well as ex-vivo studies have identified multiple variants in RYR1 and CACNA1S associated with MHS. Variant pathogenicity should be assessed based on prior clinical experience, functional studies, prevalence information, or other evidence (see CONTRAINDICATIONS, WARNINGS - Malignant Hyperthermia).

CLINICAL STUDIES

Sevoflurane was administered to a total of 3185 patients. The types of patients are summarized as follows:

Table 5. Patients Receiving Sevoflurane in Clinical Studies
Type of Patients | Number | Studied
ADULT | 2223
Cesarean Delivery |  | 29
Cardiovascular and patients at risk of myocardial ischemia |  | 246
Neurosurgical |  | 22
Hepatic impairment |  | 8
Renal impairment |  | 35
PEDIATRIC | 962

Clinical experience with these patients is described below.

Adult Anesthesia

The efficacy of sevoflurane in comparison to isoflurane, enflurane, and propofol was investigated in 3 outpatient and 25 inpatient studies involving 3591 adult patients. Sevoflurane was found to be comparable to isoflurane, enflurane, and propofol for the maintenance of anesthesia in adult patients. Patients administered sevoflurane showed shorter times (statistically significant) to some recovery events (extubation, response to command, and orientation) than patients who received isoflurane or propofol.

Mask Induction

Sevoflurane has a nonpungent odor and does not cause respiratory irritability. Sevoflurane is suitable for mask induction in adults. In 196 patients, mask induction was smooth and rapid, with complications occurring with the following frequencies: cough, 6%; breathholding, 6%; agitation, 6%; laryngospasm, 5%.

Ambulatory Surgery

Sevoflurane was compared to isoflurane and propofol for maintenance of anesthesia supplemented with N2O in two studies involving 786 adult (18-84 years of age) ASA Class I, II, or III patients. Shorter times to emergence and response to commands (statistically significant) were observed with sevoflurane compared to isoflurane and propofol.

Table 6. Recovery Parameters in Two Outpatient Surgery Studies: Least Squares Mean ± SEM
 | Sevoflurane/N 2 O | Isoflurane/N 2 O | Sevoflurane/N 2 O | Propofol/N 2 O
Mean Maintenance | 0.64 ± 0.03 | 0.66 ± 0.03 | 0.8 ± 0.5 | 7.3 ± 2.3
Anesthesia | MAC·hr. | MAC·hr. | MAC·hr. | mg/kg/hr.
Exposure ± SD | (n = 245) | (n = 249) | (n = 166) | (n = 166)
Time to Emergence (min) | 8.2 ± 0.4 (n = 246) | 9.3 ± 0.3 (n = 251) | 8.3 ± 0.7 (n = 137) | 10.4 ± 0.7 (n = 142)
Time to Respond to Commands (min) | 8.5 ± 0.4 (n = 246) | 9.8 ± 0.4 (n = 248) | 9.1 ± 0.7 (n = 139) | 11.5 ± 0.7 (n = 143)
Time to First Analgesia (min) | 45.9 ± 4.7 (n = 160) | 59.1 ± 6.0 (n = 252) | 46.1 ± 5.4 (n = 83) | 60.0 ± 4.7 (n = 88)
Time to Eligibility for | 87.6 ± 5.3 | 79.1 ± 5.2 | 103.1 ± 3.8 | 105.1 ± 3.7
Discharge from | (n = 244) | (n = 252) | (n = 139) | (n = 143)
Recovery Area (min)
n = number of patients with recording of recovery events.

Inpatient Surgery

Sevoflurane was compared to isoflurane and propofol for maintenance of anesthesia supplemented with N2O in two multicenter studies involving 741 adult ASA Class I, II or III (18-92 years of age) patients. Shorter times to emergence, command response, and first post-anesthesia analgesia (statistically significant) were observed with sevoflurane compared to isoflurane and propofol.

Table 7. Recovery Parameters in Two Inpatient Surgery Studies: Least Squares Mean ± SEM
 | Sevoflurane/N 2 O | Isoflurane/N 2 O | Sevoflurane/N 2 O | Propofol/N 2 O
Mean Maintenance | 1.27 MAC·hr. | 1.58 MAC·hr. | 1.43 MAC·hr. | 7.0 mg/kg/hr
Anesthesia | ± 0.05 | ± 0.06 | ± 0.94 | ± 2.9
Exposure ± SD | (n = 271) | (n = 282) | (n = 93) | (n = 92)
Time to Emergence (min) | 11.0 ± 0.6 (n = 270) | 16.4 ± 0.6 (n = 281) | 8.8 ± 1.2 (n = 92) | 13.2 ± 1.2 (n = 92)
Time to Respond to Commands (min) | 12.8 ± 0.7 (n = 270) | 18.4 ± 0.7 (n = 281) | 11.0 ± 1.20 (n = 92) | 14.4 ± 1.21 (n = 91)
Time to First Analgesia (min) | 46.1 ± 3.0 (n = 233) | 55.4 ± 3.2 (n = 242) | 37.8 ± 3.3 (n = 82) | 49.2 ± 3.3 (n = 79)
Time to Eligibility for Discharge from Recovery Area (min) | 139.2 ± 15.6 (n = 268) | 165.9 ± 16.3 (n = 282) | 148.4 ± 8.9 (n = 92) | 141.4 ± 8.9 (n = 92)
n = number of patients with recording of recovery events.

Pediatric Anesthesia

The concentration of sevoflurane required for maintenance of general anesthesia is age-dependent (see DOSAGE AND ADMINISTRATION). Sevoflurane or halothane was used to anesthetize 1620 pediatric patients aged 1 day to 18 years, and ASA physical status I or II (948 sevoflurane, 672 halothane). In one study involving 90 infants and children, there were no clinically significant decreases in heart rate compared to awake values at 1 MAC. Systolic blood pressure decreased 15%-20% in comparison to awake values following administration of 1 MAC sevoflurane; however, clinically significant hypotension requiring immediate intervention did not occur. Overall incidences of bradycardia [more than 20 beats/min lower than normal (80 beats/min)] in comparative studies was 3% for sevoflurane and 7% for halothane. Patients who received sevoflurane had slightly faster emergence times (12 vs. 19 minutes), and a higher incidence of post-anesthesia agitation (14% vs. 10%).

Sevoflurane (n = 91) was compared to halothane (n = 89) in a single-center study for elective repair or palliation of congenital heart disease. The patients ranged in age from 9 days to 11.8 years with an ASA physical status of II, III, and IV (18%, 68%, and 13% respectively). No significant differences were demonstrated between treatment groups with respect to the primary outcome measures: cardiovascular decompensation and severe arterial desaturation. Adverse event data was limited to the study outcome variables collected during surgery and before institution of cardiopulmonary bypass.

Mask Induction

Sevoflurane has a nonpungent odor and is suitable for mask induction in pediatric patients. In controlled pediatric studies in which mask induction was performed, the incidence of induction events is shown below (see ADVERSE REACTIONS).

Table 8. Incidence of Pediatric Induction Events
 | Sevoflurane (n = 836) | Halothane (n = 660)
Agitation | 14% | 11%
Cough | 6% | 10%
Breathholding | 5% | 6%
Secretions | 3% | 3%
Laryngospasm | 2% | 2%
Bronchospasm | < 1% | 0%
n = number of patients.

Ambulatory Surgery

Sevoflurane (n = 518) was compared to halothane (n = 382) for the maintenance of anesthesia in pediatric outpatients. All patients received N2O and many received fentanyl, midazolam, bupivacaine, or lidocaine. The time to eligibility for discharge from post-anesthesia care units was similar between agents (see CLINICAL PHARMACOLOGY, ADVERSE REACTIONS).

Cardiovascular Surgery

Coronary Artery Bypass Graft (CABG) Surgery

Sevoflurane was compared to isoflurane as an adjunct with opioids in a multicenter study of 273 patients undergoing CABG surgery. Anesthesia was induced with midazolam (0.1-0.3 mg/kg); vecuronium (0.1-0.2 mg/kg), and fentanyl (5-15 mcg/kg). Both isoflurane and sevoflurane were administered at loss of consciousness in doses of 1.0 MAC and titrated until the beginning of cardiopulmonary bypass to a maximum of 2.0 MAC. The total dose of fentanyl did not exceed 25 mcg/kg. The average MAC dose was 0.49 for sevoflurane and 0.53 for isoflurane. There were no significant differences in hemodynamics, cardioactive drug use, or ischemia incidence between the two groups. Outcome was also equivalent. In this small multicenter study, sevoflurane appears to be as effective and as safe as isoflurane for supplementation of opioid anesthesia for coronary bypass grafting.

Non-Cardiac Surgery Patients at Risk for Myocardial Ischemia

Sevoflurane-N2O was compared to isoflurane-N2O for maintenance of anesthesia in a multicenter study in 214 patients, age 40-87 years who were at mild-to-moderate risk for myocardial ischemia and were undergoing elective non-cardiac surgery. Forty-six percent (46%) of the operations were cardiovascular, with the remainder evenly divided between gastrointestinal and musculoskeletal and small numbers of other surgical procedures. The average duration of surgery was less than 2 hours. Anesthesia induction usually was performed with thiopental (2-5 mg/kg) and fentanyl (1-5 mcg/kg). Vecuronium (0.1-0.2 mg/kg) was also administered to facilitate intubation, muscle relaxation or immobility during surgery. The average MAC dose was 0.49 for both anesthetics. There was no significant difference between the anesthetic regimens for intraoperative hemodynamics, cardioactive drug use, or ischemic incidents, although only 83 patients in the sevoflurane group and 85 patients in the isoflurane group were successfully monitored for ischemia. The outcome was also equivalent in terms of adverse events, death, and postoperative myocardial infarction. Within the limits of this small multicenter study in patients at mild-to-moderate risk for myocardial ischemia, sevoflurane was a satisfactory equivalent to isoflurane in providing supplemental inhalation anesthesia to intravenous drugs.

Cesarean Section

Sevoflurane (n = 29) was compared to isoflurane (n = 27) in ASA Class I or II patients for the maintenance of anesthesia during cesarean section. Newborn evaluations and recovery events were recorded. With both anesthetics, Apgar scores averaged 8 and 9 at 1 and 5 minutes, respectively.

Use of sevoflurane as part of general anesthesia for elective cesarean section produced no untoward effects in mother or neonate. Sevoflurane and isoflurane demonstrated equivalent recovery characteristics. There was no difference between sevoflurane and isoflurane with regard to the effect on the newborn, as assessed by Apgar Score and Neurological and Adaptive Capacity Score (average = 29.5). The safety of sevoflurane in labor and vaginal delivery has not been evaluated.

Neurosurgery

Three studies compared sevoflurane to isoflurane for maintenance of anesthesia during neurosurgical procedures. In a study of 20 patients, there was no difference between sevoflurane and isoflurane with regard to recovery from anesthesia. In 2 studies, a total of 22 patients with intracranial pressure (ICP) monitors received either sevoflurane or isoflurane. There was no difference between sevoflurane and isoflurane with regard to ICP response to inhalation of 0.5, 1.0, and 1.5 MAC inspired concentrations of volatile agent during N2O-O2-fentanyl anesthesia. During progressive hyperventilation from PaCO2 = 40 to PaCO2 = 30, ICP response to hypocarbia was preserved with sevoflurane at both 0.5 and 1.0 MAC concentrations. In patients at risk for elevations of ICP, sevoflurane should be administered cautiously in conjunction with ICP-reducing maneuvers such as hyperventilation.

Hepatic Impairment

A multicenter study (2 sites) compared the safety of sevoflurane and isoflurane in 16 patients with mild-to-moderate hepatic impairment utilizing the lidocaine MEGX assay for assessment of hepatocellular function. All patients received intravenous propofol (1-3 mg/kg) or thiopental (2-7 mg/kg) for induction and succinylcholine, vecuronium, or atracurium for intubation. Sevoflurane or isoflurane was administered in either 100% O2 or up to 70% N2O/O2. Neither drug adversely affected hepatic function. No serum inorganic fluoride level exceeded 45 µM/L, but sevoflurane patients had prolonged terminal disposition of fluoride, as evidenced by longer inorganic fluoride half-life than patients with normal hepatic function (23 hours vs. 10-48 hours).

Renal Impairment

Sevoflurane was evaluated in renally impaired patients with baseline serum creatinine > 1.5 mg/dL. Fourteen patients who received sevoflurane were compared with 12 patients who received isoflurane. In another study, 21 patients who received sevoflurane were compared with 20 patients who received enflurane. Creatinine levels increased in 7% of patients who received sevoflurane, 8% of patients who received isoflurane, and 10% of patients who received enflurane. Because of the small number of patients with renal insufficiency (baseline serum creatinine greater than 1.5 mg/dL) studied, the safety of sevoflurane administration in this group has not yet been fully established. Therefore, sevoflurane should be used with caution in patients with renal insufficiency (see WARNINGS).

INDICATIONS AND USAGE

ULTANE is indicated for induction and maintenance of general anesthesia in adult and pediatric patients for inpatient and outpatient surgery.

ULTANE should be administered only by persons trained in the administration of general anesthesia. Facilities for maintenance of a patent airway, artificial ventilation, oxygen enrichment, and circulatory resuscitation must be immediately available. Since level of anesthesia may be altered rapidly, only vaporizers producing predictable concentrations of sevoflurane should be used.

CONTRAINDICATIONS

- Known or suspected genetic susceptibility to malignant hyperthermia (see WARNINGS - Malignant Hyperthermia, CLINICAL PHARMACOLOGY - Pharmacogenomics).
- Known or suspected sensitivity to sevoflurane or to other halogenated inhalational anesthetics.

WARNINGS

Risk of Renal Injury

Although data from controlled clinical studies at low flow rates are limited, findings taken from patient and animal studies suggest that there is a potential for renal injury which is presumed due to Compound A. Animal and human studies demonstrate that sevoflurane administered for more than 2 MAC·hours and at fresh gas flow rates of < 2 L/min may be associated with proteinuria and glycosuria.

While a level of Compound A exposure at which clinical nephrotoxicity might be expected to occur has not been established, it is prudent to consider all of the factors leading to Compound A exposure in humans, especially duration of exposure, fresh gas flow rate, and concentration of sevoflurane. During sevoflurane anesthesia the clinician should adjust inspired concentration and fresh gas flow rate to minimize exposure to Compound A. To minimize exposure to Compound A, sevoflurane exposure should not exceed 2 MAC·hours at flow rates of 1 to < 2 L/min. Fresh gas flow rates < 1 L/min are not recommended.

Because clinical experience in administering sevoflurane to patients with renal insufficiency (creatinine > 1.5 mg/dL) is limited, its safety in these patients has not been established.

Sevoflurane may be associated with glycosuria and proteinuria when used for long procedures at low flow rates. The safety of low flow sevoflurane on renal function was evaluated in patients with normal preoperative renal function. One study compared sevoflurane (N = 98) to an active control (N = 90) administered for ≥ 2 hours at a fresh gas flow rate of ≤ 1 Liter/minute. Per study defined criteria, one patient in the sevoflurane group developed elevations of creatinine, in addition to glycosuria and proteinuria. This patient received sevoflurane at fresh gas flow rates of ≤ 800 mL/minute. Using these same criteria, there were no patients in the active control group who developed treatment emergent elevations in serum creatinine.

Sevoflurane may present an increased risk in patients with known sensitivity to volatile halogenated anesthetic agents. KOH containing CO2 absorbents are not recommended for use with sevoflurane.

Risk of Respiratory Depression

Sevoflurane may cause respiratory depression, which may be augmented by opioid premedication or other agents causing respiratory depression. Monitor respiration and, if necessary, assist with ventilation (see PRECAUTIONS).

Risk of QT Prolongation

Reports of QT prolongation, associated with torsade de pointes (in exceptional cases, fatal), have been received. Caution should be exercised when administering sevoflurane to susceptible patients (e.g., patients with congenital Long QT Syndrome or patients taking drugs that can prolong the QT interval).

Malignant Hyperthermia

In susceptible individuals, volatile anesthetic agents, including sevoflurane, may trigger malignant hyperthermia, a skeletal muscle hypermetabolic state leading to high oxygen demand. Fatal outcomes of malignant hyperthermia have been reported. In clinical studies of ULTANE, 1 case of malignant hyperthermia was reported.

The risk of developing malignant hyperthermia increases with the concomitant administration of succinylcholine and volatile anesthetic agents. ULTANE can induce malignant hyperthermia in patients with known or suspected susceptibility based on genetic factors or family history, including those with certain inherited ryanodine receptor (RYR1) or dihydropyridine receptor (CACNA1S) variants (see CONTRAINDICATIONS, CLINICAL PHARMACOLOGY - Pharmacogenomics).

Signs consistent with malignant hyperthermia may include hyperthermia, hypoxia, hypercapnia, muscle rigidity (e.g., jaw muscle spasm), tachycardia (e.g., particularly that unresponsive to deepening anesthesia or analgesic medication administration), tachypnea, cyanosis, arrhythmias, hypovolemia, and hemodynamic instability. Skin mottling, coagulopathies, and renal failure may occur later in the course of the hypermetabolic process.

Successful treatment of malignant hyperthermia depends on early recognition of the clinical signs. If malignant hyperthermia is suspected, discontinue all triggering agents (i.e., volatile anesthetic agents and succinylcholine), administer intravenous dantrolene sodium, and initiate supportive therapies. Consult prescribing information for intravenous dantrolene sodium for additional information on patient management. Supportive therapies include administration of supplemental oxygen and respiratory support based on clinical need, maintenance of hemodynamic stability and adequate urinary output, management of fluid and electrolyte balance, correction of acid base derangements, and institution of measures to control rising temperature.

Perioperative Hyperkalemia

Use of inhaled anesthetic agents has been associated with rare increases in serum potassium levels that have resulted in cardiac arrhythmias and death in pediatric patients during the postoperative period. Patients with latent as well as overt neuromuscular disease, particularly Duchenne muscular dystrophy, appear to be most vulnerable. Concomitant use of succinylcholine has been associated with most, but not all, of these cases. These patients also experienced significant elevations in serum creatine kinase levels and, in some cases, changes in urine consistent with myoglobinuria. Despite the similarity in presentation to malignant hyperthermia, none of these patients exhibited signs or symptoms of muscle rigidity or hypermetabolic state. Early and aggressive intervention to treat the hyperkalemia and resistant arrhythmias is recommended as is subsequent evaluation for latent neuromuscular disease.

Pediatric Neurotoxicity

Published animal studies demonstrate that the administration of anesthetic and sedation drugs that block NMDA receptors and/or potentiate GABA activity increase neuronal apoptosis in the developing brain and result in long-term cognitive deficits when used for longer than 3 hours. The clinical significance of these findings is not clear. However, based on the available data, the window of vulnerability to these changes is believed to correlate with exposures in the third trimester of gestation through the first several months of life, but may extend out to approximately three years of age in humans (see PRECAUTIONS - Pregnancy, PRECAUTIONS - Pediatric Use, ANIMAL TOXICOLOGY AND/OR PHARMACOLOGY).

Some published studies in children suggest that similar deficits may occur after repeated or prolonged exposures to anesthetic agents early in life and may result in adverse cognitive or behavioral effects. These studies have substantial limitations, and it is not clear if the observed effects are due to the anesthetic/sedation drug administration or other factors such as the surgery or underlying illness.

Anesthetic and sedation drugs are a necessary part of the care of children needing surgery, other procedures, or tests that cannot be delayed, and no specific medications have been shown to be safer than any other. Decisions regarding the timing of any elective procedures requiring anesthesia should take into consideration the benefits of the procedure weighed against the potential risks.

Bradycardia in Down Syndrome

Episodes of severe bradycardia and cardiac arrest, not related to underlying congenital heart disease, have been reported during anesthesia induction with sevoflurane in pediatric patients with Down syndrome. In most cases, bradycardia improved with decreasing the concentration of sevoflurane, manipulating the airway, or administering an anticholinergic or epinephrine.

During induction, closely monitor heart rate, and consider incrementally increasing the inspired sevoflurane concentration until a suitable level of anesthesia is achieved. Consider having an anticholinergic and epinephrine available when administering sevoflurane for induction in this patient population.

Risk of Driving and Operating Machinery

Performance of activities requiring mental alertness, such as driving or operating machinery, may be impaired after sevoflurane anesthesia.

PRECAUTIONS

During the maintenance of anesthesia, increasing the concentration of sevoflurane produces dose-dependent decreases in blood pressure. Due to sevoflurane's insolubility in blood, these hemodynamic changes may occur more rapidly than with other volatile anesthetics. Excessive decreases in blood pressure or respiratory depression may be related to depth of anesthesia and may be corrected by decreasing the inspired concentration of sevoflurane.

Rare cases of seizures have been reported in association with sevoflurane use (see PRECAUTIONS - Pediatric Use, ADVERSE REACTIONS).

The recovery from general anesthesia should be assessed carefully before a patient is discharged from the post-anesthesia care unit.

Information for Patients

Risk of Driving and Operating Machinery

Advise patients that performance of activities requiring mental alertness, such as driving or operating machinery, may be impaired after sevoflurane anesthesia (see WARNINGS).

Effect of anesthetic and sedation drugs on early brain development

Studies conducted in young animals and children suggest repeated or prolonged use of general anesthetic or sedation drugs in children younger than 3 years may have negative effects on their developing brains. Discuss with parents and caregivers the benefits, risks, and timing and duration of surgery or procedures requiring anesthetic and sedation drugs (see WARNINGS - Pediatric Neurotoxicity).

Drug Interactions

In clinical studies, no significant adverse reactions occurred with other drugs commonly used in the perioperative period, including central nervous system depressants, autonomic drugs, skeletal muscle relaxants, anti-infective agents, hormones and synthetic substitutes, blood derivatives, and cardiovascular drugs.

Epinephrine

Epinephrine administered with sevoflurane may increase the risk of ventricular arrhythmias. Monitor the electrocardiogram and blood pressure and ensure emergency medications to treat ventricular arrhythmias are readily available.

Calcium antagonists

Sevoflurane may lead to marked hypotension in patients treated with calcium antagonists. Blood pressure should be closely monitored and emergency medications to treat hypotension should be readily available when calcium antagonists are used concomitantly with sevoflurane.

In animals, impairment of atrioventricular conduction has been observed when verapamil and sevoflurane are administered concomitantly.

Succinylcholine

See WARNINGS - Perioperative Hyperkalemia.

Non-selective MAO-inhibitors

Concomitant use of MAO inhibitors and inhalational anesthetics may increase the risk of hemodynamic instability during surgery or medical procedures.

Intravenous Anesthetics

Sevoflurane administration is compatible with barbiturates, propofol, and other commonly used intravenous anesthetics.

Benzodiazepines and Opioids

Benzodiazepines and opioids would be expected to decrease the MAC of sevoflurane in the same manner as with other inhalational anesthetics. Sevoflurane administration is compatible with benzodiazepines and opioids as commonly used in surgical practice.

Nitrous Oxide

As with other halogenated volatile anesthetics, the anesthetic requirement for sevoflurane is decreased when administered in combination with nitrous oxide. Using 50% N2O, the MAC equivalent dose requirement is reduced approximately 50% in adults, and approximately 25% in pediatric patients (see DOSAGE AND ADMINISTRATION).

Neuromuscular Blocking Agents

As is the case with other volatile anesthetics, sevoflurane increases both the intensity and duration of neuromuscular blockade induced by nondepolarizing muscle relaxants. When used to supplement alfentanil-N2O anesthesia, sevoflurane and isoflurane equally potentiate neuromuscular block induced with pancuronium, vecuronium or atracurium. Therefore, during sevoflurane anesthesia, the dosage adjustments for these muscle relaxants are similar to those required with isoflurane.

Potentiation of neuromuscular blocking agents requires equilibration of muscle with delivered partial pressure of sevoflurane. Reduced doses of neuromuscular blocking agents during induction of anesthesia may result in delayed onset of conditions suitable for endotracheal intubation or inadequate muscle relaxation.

Among available nondepolarizing agents, only vecuronium, pancuronium and atracurium interactions have been studied during sevoflurane anesthesia. In the absence of specific guidelines:

1. For endotracheal intubation, do not reduce the dose of nondepolarizing muscle relaxants.
2. During maintenance of anesthesia, the required dose of nondepolarizing muscle relaxants is likely to be reduced compared to that during N2O/opioid anesthesia. Administration of supplemental doses of muscle relaxants should be guided by the response to nerve stimulation.

The effect of sevoflurane on the duration of depolarizing neuromuscular blockade induced by succinylcholine has not been studied.

Hepatic Function

Results of evaluations of laboratory parameters (e.g., ALT, AST, alkaline phosphatase, and total bilirubin, etc.), as well as investigator-reported incidence of adverse events relating to liver function, demonstrate that sevoflurane can be administered to patients with normal or mild-to-moderately impaired hepatic function. However, patients with severe hepatic dysfunction were not investigated.

Occasional cases of transient changes in postoperative hepatic function tests were reported with both sevoflurane and reference agents. Sevoflurane was found to be comparable to isoflurane regarding these changes in hepatic function.

Cases of mild, moderate, and severe hepatic dysfunction or hepatitis (e.g., jaundice associated with fever and/or eosinophilia) after anesthesia with sevoflurane have been reported. Clinical judgement should be exercised when sevoflurane is used in patients with underlying hepatic conditions or under treatment with drugs known to cause hepatic dysfunction (see ADVERSE REACTIONS).

It has been reported that previous exposure to halogenated hydrocarbon anesthetics may increase the potential for hepatic injury.

Desiccated CO 2 Absorbents

An exothermic reaction occurs when sevoflurane is exposed to CO2 absorbents. This reaction is increased when the CO2 absorbent becomes desiccated, such as after an extended period of dry gas flow through the CO2 absorbent canisters. Rare cases of extreme heat, smoke, and/or spontaneous fire in the anesthesia breathing circuit have been reported during sevoflurane use in conjunction with the use of desiccated CO2 absorbent, specifically those containing potassium hydroxide (e.g., Baralyme). KOH containing CO2 absorbents are not recommended for use with sevoflurane. An unusually delayed rise or unexpected decline of inspired sevoflurane concentration compared to the vaporizer setting may be associated with excessive heating of the CO2 absorbent and chemical breakdown of sevoflurane.

As with other inhalational anesthetics, degradation and production of degradation products can occur when sevoflurane is exposed to desiccated absorbents. When a clinician suspects that the CO2 absorbent may be desiccated, it should be replaced. The color indicator of most CO2 absorbents may not change upon desiccation. Therefore, the lack of significant color change should not be taken as an assurance of adequate hydration. CO2 absorbents should be replaced routinely regardless of the state of the color indicator.

Carcinogenesis, Mutagenesis, Impairment of Fertility

Carcinogenesis

Studies on carcinogenesis have not been performed for either sevoflurane or Compound A.

Mutagenesis

No mutagenic effect of sevoflurane was noted in the Ames test, mouse micronucleus test, mouse lymphoma mutagenicity assay, human lymphocyte culture assay, mammalian cell transformation assay, ^32P DNA adduct assay, and no chromosomal aberrations were induced in cultured mammalian cells.

Similarly, no mutagenic effect of Compound A was noted in the Ames test, the Chinese hamster chromosomal aberration assay and the in vivo mouse micronucleus assay. However, positive responses were observed in the human lymphocyte chromosome aberration assay. These responses were seen only at high concentrations and in the absence of metabolic activation (human S-9).

Impairment of Fertility

In a study in which male rats were treated with sevoflurane (0.22%, 0.66%, 1.1%, or 2.2% equals 0.1, 0.3, 0.5, or 1.0 MAC) three hours per day every other day starting 64 days prior to mating and female rats were treated with the same dosing regimen 14 days prior to mating until Gestation Day 7, there was no clear impact on male or female fertility.

Pregnancy

Risk Summary

There are no adequate and well-controlled studies in pregnant women.

In animal reproduction studies, reduced fetal weights were noted following exposure to 1 MAC sevoflurane for three hours a day during organogenesis. Developmental and reproductive toxicity studies of sevoflurane in animals in the presence of strong alkalies (i.e., degradation of sevoflurane and production of Compound A) have not been conducted. Published studies in pregnant primates demonstrate that the administration of anesthetic and sedation drugs that block NMDA receptors and/or potentiate GABA activity during the period of peak brain development increases neuronal apoptosis in the developing brain of the offspring when used for longer than 3 hours. There are no data on pregnancy exposures in primates corresponding to periods prior to the third trimester in humans.

The estimated background risk of major birth defects and miscarriage for the indicated population is unknown. All pregnancies have a background risk of birth defect, loss, or other adverse outcomes. In the U.S. general population, the estimated background risk of major birth defects and miscarriage in clinically recognized pregnancies is 2-4% and 15-20%, respectively.

Data

Animal Data

Pregnant rats were treated with sevoflurane (0.22%, 0.66%, or 2.2% equals 0.1, 0.3, or 1.0 MAC) without CO2 absorbent for three hours per day during organogenesis (from Gestation Day 7 to 17). Fetuses obtained by Cesarean section were examined on Gestation Day 20 while some animals were maintained for littering and pups were examined for adverse effects. There were no adverse effects on fetuses at 0.3 MAC. Reduced fetal body weights and increased skeletal variations such as delayed ossifications in the presence of maternal toxicity (reduced food and water intake and body weight of the dams) were noted at 1 MAC. In dams allowed to litter, reduced pup bodyweight gain and evidence of developmental delays (slight delay in eyelid opening and increased incidence of nonreactive animals in the visual placing reflex test) were noted in the 1.0 MAC treatment group.

Pregnant rabbits were treated with sevoflurane (0.1, 0.3, or 1.0 MAC) without CO2 absorbent for three hours per day during organogenesis (from Gestation Day 6 to 18). There were no adverse effects on the fetus at any dose; the mid- and high-dose produced a 5% and 6% decrease in maternal body weight, respectively.

In another study, pregnant rats were administered sevoflurane (0.1, 0.3, or 1.0 MAC) from Gestation Day 17 to Postnatal Day 21. Pup body weights were reduced in the 1.0 MAC treatment group in the absence of maternal toxicity. There was no effect of sevoflurane on sensory function (visual, auditory, nociception, righting reflexes), motor (roto-rod), open field test, or learning tasks (shuttle box avoidance and water T-maze).

In a published study in primates, administration of an anesthetic dose of ketamine for 24 hours on Gestation Day 122 increased neuronal apoptosis in the developing brain of the fetus. In other published studies, administration of either isoflurane or propofol for 5 hours on Gestation Day 120 resulted in increased neuronal and oligodendrocyte apoptosis in the developing brain of the offspring. With respect to brain development, this time period corresponds to the third trimester of gestation in the human. The clinical significance of these findings is not clear; however, studies in juvenile animals suggest neuroapoptosis correlates with long-term cognitive deficits (see WARNINGS - Pediatric Neurotoxicity, PRECAUTIONS - Pediatric Use, ANIMAL TOXICOLOGY AND/OR PHARMACOLOGY).

Labor and Delivery

Sevoflurane has been used in clinical studies, as part of general anesthesia for elective cesarean section, in 29 women. There were no untoward effects in mother or neonate (see CLINICAL STUDIES). The safety of sevoflurane in labor and delivery has not been demonstrated.

Sevoflurane can cause uterine smooth muscle relaxation and may contribute to uterine atony.

Nursing Mothers

It is not known whether sevoflurane or its metabolites are present in human milk. To minimize infant exposure to sevoflurane or its metabolites, a nursing mother may temporarily pump, and discard breast milk produced during the first 24 hours after administration of sevoflurane. Exercise caution when administering sevoflurane to a nursing mother.

Geriatric Use

MAC decreases with increasing age. The average concentration of sevoflurane to achieve MAC in an 80 year old is approximately 50% of that required in a 20 year old.

Pediatric Use

Induction and maintenance of general anesthesia with sevoflurane have been established in controlled clinical studies in pediatric patients aged 1 to 18 years (see CLINICAL STUDIES, ADVERSE REACTIONS). Sevoflurane has a nonpungent odor and is suitable for mask induction in pediatric patients.

The concentration of sevoflurane required for maintenance of general anesthesia is age dependent. When used in combination with nitrous oxide, the MAC equivalent dose of sevoflurane should be reduced in pediatric patients. MAC in premature infants has not been determined (see PRECAUTIONS - Drug Interactions, DOSAGE AND ADMINISTRATION for recommendations in pediatric patients 1 day of age and older).

The use of sevoflurane has been associated with seizures (see PRECAUTIONS, ADVERSE REACTIONS). The majority of these have occurred in children and young adults starting from 2 months of age, most of whom had no predisposing risk factors. Clinical judgement should be exercised when using sevoflurane in patients who may be at risk for seizures.

Cases of life-threatening ventricular arrhythmias have been reported in pediatric patients with Pompe disease (also commonly known as glycogen storage disease type II or acid maltase deficiency). In a published case series about a clinical trial of patients with infantile-onset Pompe disease, six percent of patients (9 of 139, with 6 of 9 having received sevoflurane) experienced arrhythmias after induction of anesthesia. Reported arrhythmias included severe bradycardia, torsade de pointes, and fatal ventricular fibrillation, which usually resolved after treatment with pharmacologic agents and defibrillation. Avoid induction and maintenance of anesthesia using sole agents, such as sevoflurane, that decrease systemic vascular resistance or diastolic blood pressure.

Published juvenile animal studies demonstrate that the administration of anesthetic and sedation drugs, such as ULTANE, that either block NMDA receptors or potentiate the activity of GABA during the period of rapid brain growth or synaptogenesis, results in widespread neuronal and oligodendrocyte cell loss in the developing brain and alterations in synaptic morphology and neurogenesis. Based on comparisons across species, the window of vulnerability to these changes is believed to correlate with exposures in the third trimester of gestation through the first several months of life, but may extend out to approximately 3 years of age in humans.

In primates, exposure to 3 hours of ketamine that produced a light surgical plane of anesthesia did not increase neuronal cell loss; however, treatment regimens of 5 hours or longer of isoflurane increased neuronal cell loss. Data from isoflurane-treated rodents and ketamine-treated primates suggest that the neuronal and oligodendrocyte cell losses are associated with prolonged cognitive deficits in learning and memory. The clinical significance of these nonclinical findings is not known, and healthcare providers should balance the benefits of appropriate anesthesia in pregnant women, neonates, and young children who require procedures with the potential risks suggested by the nonclinical data (see WARNINGS - Pediatric Neurotoxicity, PRECAUTIONS - Pregnancy, ANIMAL TOXICOLOGY AND/OR PHARMACOLOGY).

Use in Pediatric Patients with Down Syndrome

See WARNINGS - Bradycardia in Down Syndrome.

ADVERSE REACTIONS

Clinical Trials Experience

Adverse events are derived from controlled clinical studies conducted in the United States, Canada, and Europe. The reference drugs were isoflurane, enflurane, and propofol in adults and halothane in pediatric patients. The studies were conducted using a variety of premedications, other anesthetics, and surgical procedures of varying length. Most adverse events reported were mild and transient, and may reflect the surgical procedures, patient characteristics (including disease) and/or medications administered.

Of the 5182 patients enrolled in the clinical studies, 2906 were exposed to sevoflurane, including 118 adults and 507 pediatric patients who underwent mask induction. Each patient was counted once for each type of adverse event. Adverse events reported in patients in clinical studies and considered to be possibly or probably related to sevoflurane are presented within each body system in order of decreasing frequency in the following listings. One case of malignant hyperthermia was reported in pre-registration clinical studies.

Adverse Events During the Induction Period (from Onset of Anesthesia by Mask Induction to Surgical Incision) Incidence > 1%

Adult Patients (N = 118)

Cardiovascular

Bradycardia 5%, Hypotension 4%, Tachycardia 2%

Nervous System

Agitation 7%

Respiratory System

Laryngospasm 8%, Airway obstruction 8%, Breathholding 5%, Cough Increased 5%

Pediatric Patients (N = 507)

Cardiovascular

Tachycardia 6%, Hypotension 4%

Nervous System

Agitation 15%

Respiratory System

Breathholding 5%, Cough Increased 5%, Laryngospasm 3%, Apnea 2%

Digestive System

Increased salivation 2%

Adverse Events During Maintenance and Emergence Periods, Incidence > 1% (N = 2906)

Body as a whole

Fever 1%, Shivering 6%, Hypothermia 1%, Movement 1%, Headache 1%

Cardiovascular

Hypotension 11%, Hypertension 2%, Bradycardia 5%, Tachycardia 2%

Nervous System

Somnolence 9%, Agitation 9%, Dizziness 4%, Increased salivation 4%

Digestive System

Nausea 25%, Vomiting 18%

Respiratory System

Cough increased 11%, Breathholding 2%, Laryngospasm 2%

Adverse Events, All Patients in Clinical Studies (N = 2906), All Anesthetic Periods, Incidence < 1% (Reported in 3 or More Patients)

Body as a whole

Asthenia, Pain

Cardiovascular

Arrhythmia, Ventricular Extrasystoles, Supraventricular Extrasystoles, Complete AV Block, Bigeminy, Hemorrhage, Inverted T Wave, Atrial Fibrillation, Atrial Arrhythmia, Second Degree AV Block, Syncope, S-T Depressed

Nervous System

Crying, Nervousness, Confusion, Hypertonia, Dry Mouth, Insomnia

Respiratory System

Sputum Increased, Apnea, Hypoxia, Wheezing, Bronchospasm, Hyperventilation, Pharyngitis, Hiccup, Hypoventilation, Dyspnea, Stridor

Metabolism and Nutrition

Increases in LDH, AST, ALT, BUN, Alkaline Phosphatase, Creatinine, Bilirubinemia, Glycosuria, Fluorosis, Albuminuria, Hypophosphatemia, Acidosis, Hyperglycemia

Hemic and Lymphatic System

Leucocytosis, Thrombocytopenia

Skin and Special Senses

Amblyopia, Pruritus, Taste Perversion, Rash, Conjunctivitis

Urogenital

Urination Impaired, Urine Abnormality, Urinary Retention, Oliguria

See WARNINGS for information regarding malignant hyperthermia.

Postmarketing Experience

The following adverse events have been identified during post-approval use of Ultane (sevoflurane USP). Due to the spontaneous nature of these reports, the actual incidence and relationship of Ultane to these events cannot be established with certainty.

Central Nervous System

- Seizures: Postmarketing reports indicate that sevoflurane use has been associated with seizures. The majority of cases were in children and young adults, most of whom had no medical history of seizures. Several cases reported no concomitant medications, and at least one case was confirmed by EEG. Although many cases were single seizures that resolved spontaneously or after treatment, cases of multiple seizures have also been reported. Seizures have occurred during, or soon after sevoflurane induction, during emergence, and during post-operative recovery up to a day following anesthesia.
- Delirium

Cardiac

- Cardiac arrest
- QT prolongation associated with Torsade de Pointe
- Bradycardia in patients with Down syndrome

Pulmonary

- Diffuse Alveolar Hemorrhage: Hemoptysis, shortness of breath with chest X-ray findings, and increasing aliquots of frank blood on bronchoalveolar lavage have been reported following exposure to sevoflurane and in the absence of observed airway obstruction.

Hepatic

- Cases of mild, moderate and severe post-operative hepatic dysfunction or hepatitis with or without jaundice have been reported. Histological evidence was not provided for any of the reported hepatitis cases. In most of these cases, patients had underlying hepatic conditions or were under treatment with drugs known to cause hepatic dysfunction. Most of the reported events were transient and resolved spontaneously (see PRECAUTIONS).
- Hepatic necrosis
- Hepatic failure

Other

- Malignant hyperthermia (see CONTRAINDICATIONS, WARNINGS)
- Allergic reactions, such as rash, urticaria, pruritus, bronchospasm, and anaphylactic reactions (see CONTRAINDICATIONS)
- Reports of hypersensitivity (including contact dermatitis, rash, dyspnea, wheezing, chest discomfort, swelling face, or anaphylactic reaction) have been received, particularly in association with long-term occupational exposure to inhaled anesthetic agents, including sevoflurane (see SAFETY AND HANDLING - Occupational Caution).

Laboratory Findings

- Transient elevations in glucose, liver function tests, and white blood cell count may occur as with use of other anesthetic agents.

OVERDOSAGE

In the event of overdosage, or what may appear to be overdosage, the following action should be taken: discontinue administration of sevoflurane, maintain a patent airway, initiate assisted or controlled ventilation with oxygen, and maintain adequate cardiovascular function.

DOSAGE AND ADMINISTRATION

The concentration of sevoflurane being delivered from a vaporizer should be known. This may be accomplished by using a vaporizer calibrated specifically for sevoflurane. The administration of general anesthesia must be individualized based on the patient's response.

Replacement of Desiccated CO 2 Absorbents

When a clinician suspects that the CO2 absorbent may be desiccated, it should be replaced. The exothermic reaction that occurs with sevoflurane and CO2 absorbents is increased when the CO2 absorbent becomes desiccated, such as after an extended period of dry gas flow through the CO2 absorbent canisters (see PRECAUTIONS).

Pre-anesthetic Medication

No specific premedication is either indicated or contraindicated with sevoflurane. The decision as to whether or not to premedicate and the choice of premedication is left to the discretion of the anesthesiologist.

Induction

Sevoflurane has a nonpungent odor and does not cause respiratory irritability; it is suitable for mask induction in pediatrics and adults.

Maintenance

Surgical levels of anesthesia can usually be achieved with concentrations of 0.5 - 3% sevoflurane with or without the concomitant use of nitrous oxide. Sevoflurane can be administered with any type of anesthesia circuit.

Table 9. MAC Values for Adults and Pediatric Patients According to Age
Age of Patient (years) | Sevoflurane in Oxygen | Sevoflurane in
 |  | 65% N 2 O/35% O 2
0 - 1 months # | 3.3%
1 - < 6 months | 3.0%
6 months - < 3 years | 2.8% | 2.0%@
3 - 12 | 2.5%
25 | 2.6% | 1.4%
40 | 2.1% | 1.1%
60 | 1.7% | 0.9%
80 | 1.4% | 0.7%
# Neonates are full-term gestational age. MAC in premature infants has not been determined.
@ In 1 - < 3 year old pediatric patients, 60% N2O/40% O2 was used.

HOW SUPPLIED

ULTANE (sevoflurane), Volatile Liquid for Inhalation, is packaged in amber colored bottles containing 250 mL sevoflurane, List 4456, NDC # 0074-4456-51 (plastic).

SAFETY AND HANDLING

Occupational Caution

There is no specific work exposure limit established for sevoflurane. However, the National Institute for Occupational Safety and Health has recommended an 8 hour time-weighted average limit of 2 ppm for halogenated anesthetic agents in general (0.5 ppm when coupled with exposure to N2O) (see ADVERSE REACTIONS).

Storage

Store at controlled room temperature, 15° - 30°C (59° - 86°F). See USP.

ANIMAL TOXICOLOGY AND/OR PHARMACOLOGY

Published studies in animals demonstrate that the use of anesthetic agents during the period of rapid brain growth or synaptogenesis results in widespread neuronal and oligodendrocyte cell loss in the developing brain and alterations in synaptic morphology and neurogenesis. Based on comparisons across species, the window of vulnerability to these changes is believed to correlate with exposures in the third trimester through the first several months of life, but may extend out to approximately 3 years of age in humans.

In primates, exposure to 3 hours of an anesthetic regimen that produced a light surgical plane of anesthesia did not increase neuronal cell loss; however, treatment regimens of 5 hours or longer increased neuronal cell loss. Data in rodents and in primates suggest that the neuronal and oligodendrocyte cell losses are associated with subtle but prolonged cognitive deficits in learning and memory. The clinical significance of these nonclinical findings is not known, and healthcare providers should balance the benefits of appropriate anesthesia in pregnant women, neonates and young children who require procedures against the potential risks suggested by the nonclinical data (see WARNINGS - Pediatric Neurotoxicity, PRECAUTIONS - Pregnancy, PRECAUTIONS - Pediatric Use).

Product of Japan
Product inquiries should be directed to AbbVie Inc., North Chicago, IL 60064, USA

Manufactured by:
AbbVie Inc., North Chicago, IL 60064, USA under license from Maruishi Pharmaceutical
Company LTD. 2-3-5, Fushimi-machi, Chuo-Ku, Osaka, Japan.

Novaplus is a registered trademark of Vizient, Inc.

© 2025 AbbVie. All rights reserved.
ULTANE and its design are trademarks of AbbVie Inc.
20090726 February 2025

PACKAGE LABEL

NDC 0074-4456-51

ULTANE®

sevoflurane

250 mL

INHALATION ANESTHETIC

Rx only

Product of Japan

Product inquiries should be directed

to AbbVie Inc.,

North Chicago, IL 60064 USA

novaplusTM